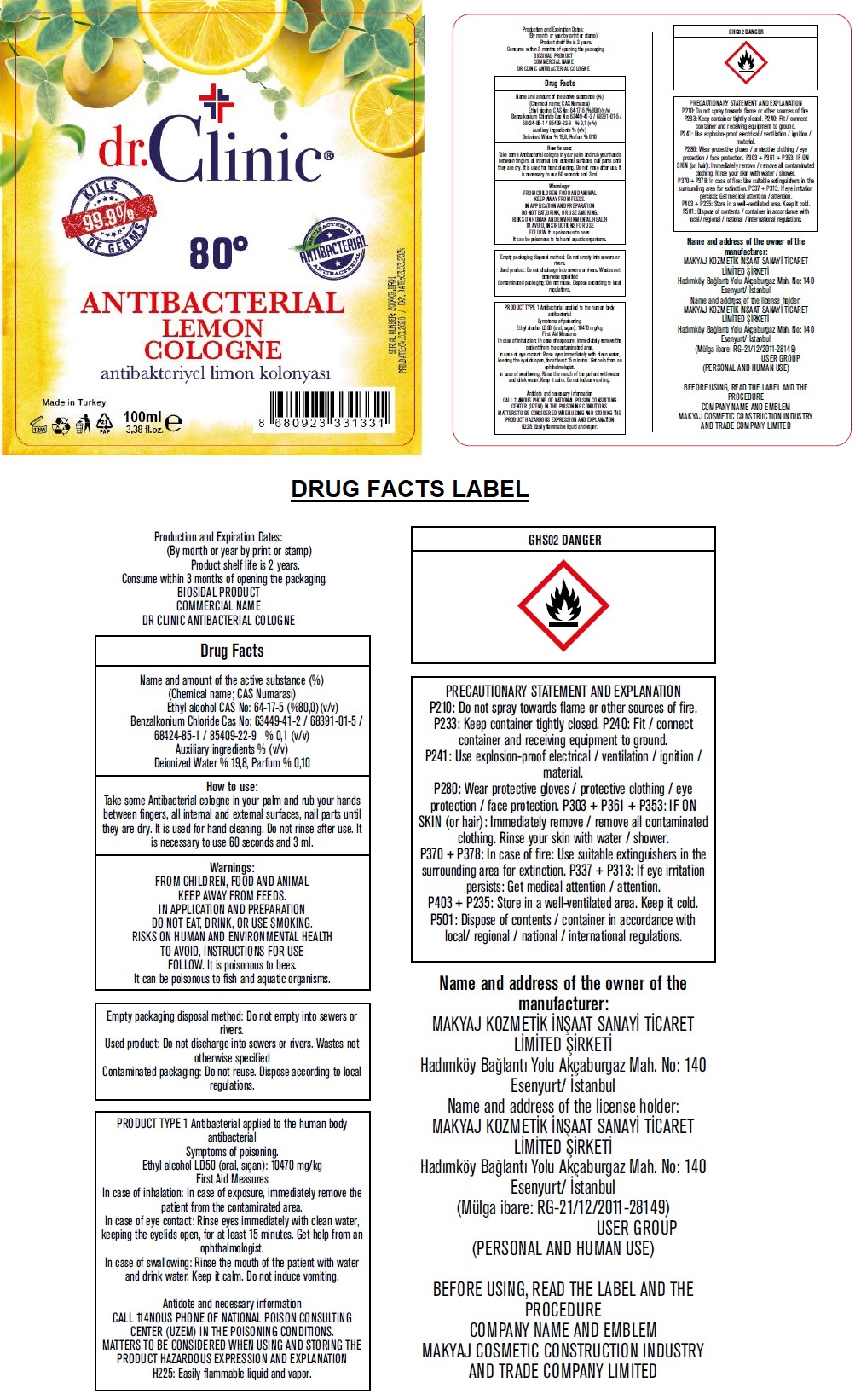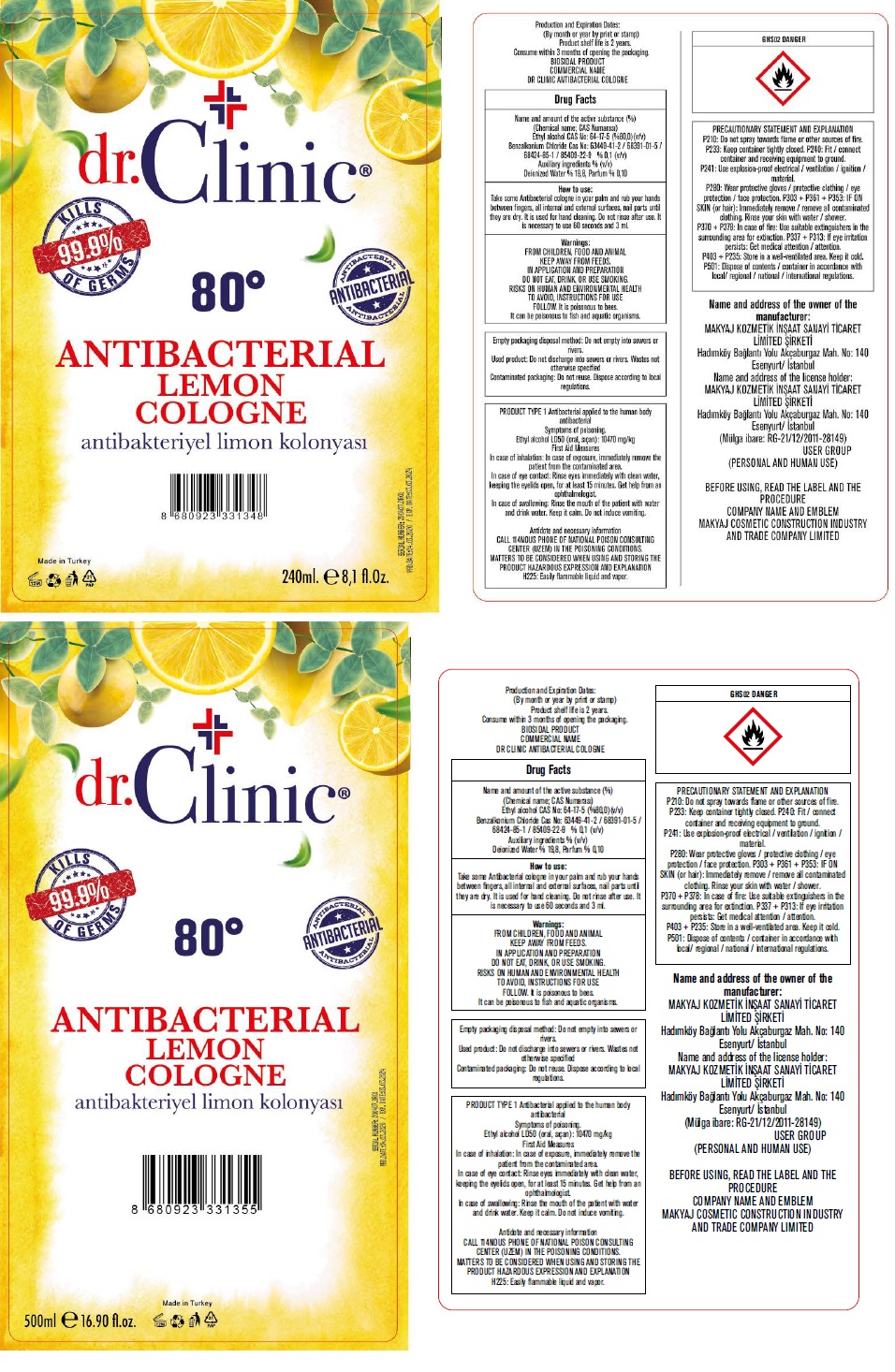 DRUG LABEL: DR.CLINIC ANTIBACTERIAL COLOGNE
NDC: 76725-102 | Form: LIQUID
Manufacturer: MAKYAJ KOZMETIK INSAAT SANAYI VE TICARET LIMITED SIRKETI
Category: otc | Type: HUMAN OTC DRUG LABEL
Date: 20200513

ACTIVE INGREDIENTS: ALCOHOL 80 mL/100 mL; BENZALKONIUM CHLORIDE 0.1 g/100 mL
INACTIVE INGREDIENTS: WATER

dr.CLINIC® ANTIBACTERIAL LEMON COLOGNE

Active ingredients

Ethyl alcohol 80% (v/v)

Benzalkonium Chloride 0.1% (v/v)

Purpose

Antibacterial

Inactive ingredients

Deionized Water, Parfum

Use:

Antibacterial applied to the human body

Direction:

Take some Antibacterial cologne in your palm and rub your hands between fingers, all internal and external surfaces, nail parts until they are dry. It is used for hand cleaning. Do not rinse after use. It is necessary to use 60 seconds and 3 ml.

Warnings:

IN APPLICATION AND PREPARATION DO NOT EAT, DRINK, OR USE SMOKING. RISKS ON HUMAN AND ENVIRONMENTAL HEALTH TO AVOID, INSTRUCTIONS FOR USE FOLLOW. It is poisonous to bees. It can be poisonous to fish and aquatic organisms.

Empty packaging disposal method: Do not empty into sewers or rivers.

Used product: Do not discharge into sewers or rivers. Wastes not otherwise specified

Contaminated packaging: Do not reuse. Dispose according to local regulations.

Symptoms of poisoning.

Ethyl alcohol LD50 (oral): 10470 mg/kg

First Aid Measures

In case of inhalation: In case of exposure, immediately remove the patient from the contaminated area.

In case of eye contact: Rinse eyes immediately with clean water, keeping the eyelids open, for at least 15 minutes. Get help from an ophthalmologist.

In case of swallowing: Rinse the mouth of the patient with water and drink water. Keep it calm. Do not induce vomiting.

Antidote and necessary information

CALL 114NOUS PHONE OF NATIONAL POISON CONSULTING CENTER (UZEM) IN THE POISONING CONDITIONS. MATTERS TO BE CONSIDERED WHEN USING AND STORING THE PRODUCT HAZARDOUS EXPRESSION AND EXPLANATION

H225: Easily flammable liquid and vapor.

GHS02 DANGER

KEEP OUT OF REACH OF CHILDREN

FROM CHILDREN, FOOD AND ANIMAL KEEP AWAY FROM FEEDS.

PRECAUTIONS

PRECAUTIONARY STATEMENT AND EXPLANATION

P210: Do not spray towards flame or other sources of fire.

P233: Keep container tightly closed.

P240: Fit / connect container and receiving equipment to ground.

P241: Use explosion-proof electrical / ventilation / ignition / material.

P280: Wear protective gloves / protective clothing / eye protection / face protection.

P303 + P361 + P353: IF ON SKIN (or hair): Immediately remove / remove all contaminated clothing. Rinse your skin with water / shower.

P370 + P378: In case of fire: Use suitable extinguishers in the surrounding area for extinction.

P337 + P313: If eye irritation persists: Get medical attention / attention.

P403 + P235: Store in a well-ventilated area. Keep it cold.

P501: Dispose of contents / container in accordance with local/ regional / national / international regulations.

80° ANTIBACTERIAL

KILLS 99.9% OF GERMS

Made in Turkey

Production and Expiration Dates: (By month or year by print or stamp)

Product shelf life is 2 years. Consume within 3 months of opening the packaging.

BIOSIDAL PRODUCT

COMMERCIAL NAME
DR CLINIC ANTIBACTERIAL COLOGNE

Name and address of the owner of the manufacturer:

MAKYAJ KOZMETIK INSAAT SANAYI TICARET LIMITED SIRKETI

Hadımköy Baglantı Yolu Akçaburgaz Mah. No: 140 Esenyurt/ Istanbul

Name and address of the license holder:

MAKYAJ KOZMETIK INSAAT SANAYI TICARET LIMITED SIRKETI

Hadımköy Baglantı Yolu Akçaburgaz Mah. No: 140 Esenyurt/ Istanbul
(Mülga ibare: RG-21/12/2011-28149)

USER GROUP (PERSONAL AND HUMAN USE)

BEFORE USING, READ THE LABEL AND THE PROCEDURE
COMPANY NAME AND EMBLEM

MAKYAJ COSMETIC CONSTRUCTION INDUSTRY AND TRADE COMPANY LIMITED